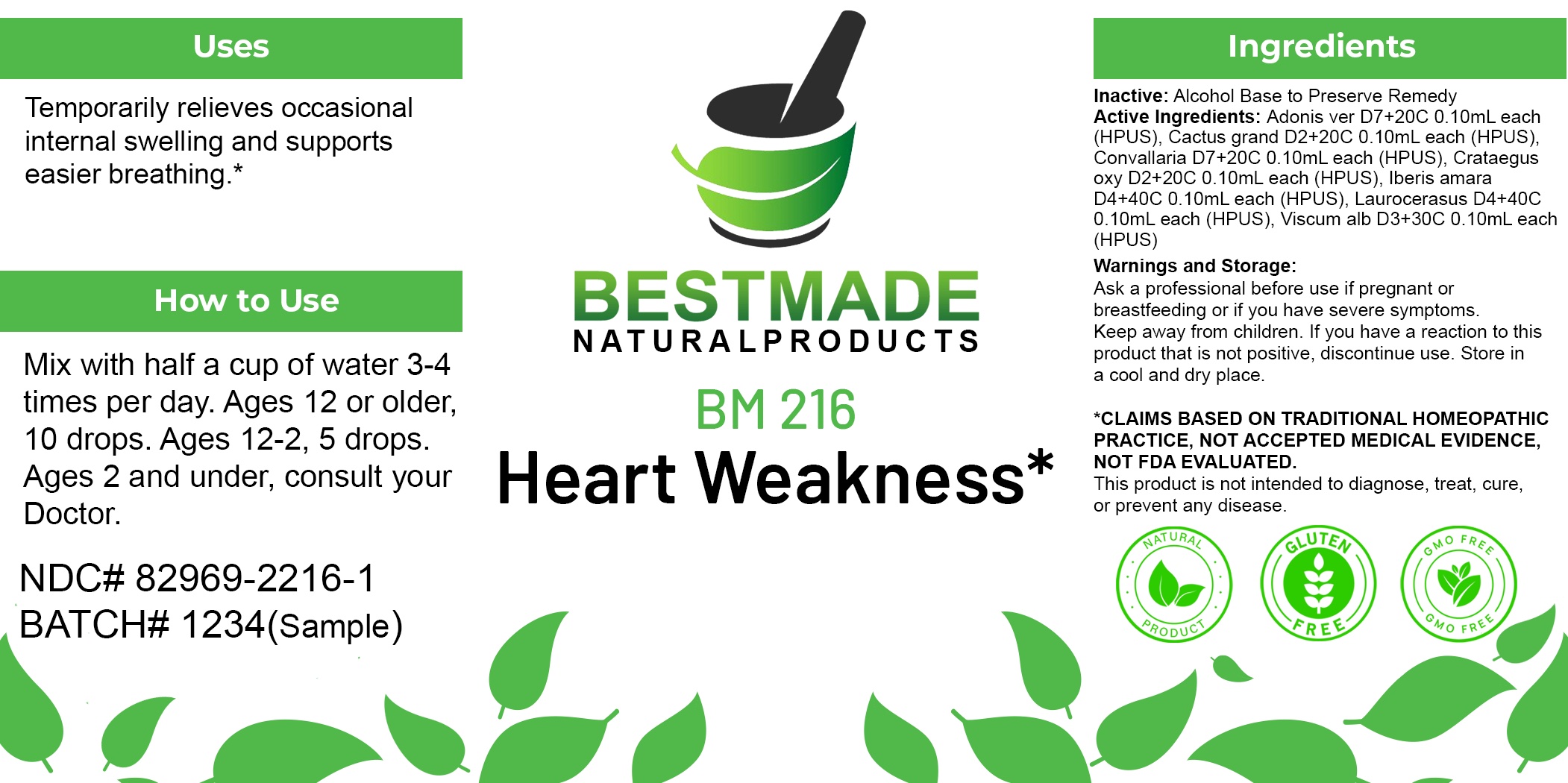 DRUG LABEL: Bestmade Natural Products BM216
NDC: 82969-2216 | Form: LIQUID
Manufacturer: Bestmade Natural Products
Category: homeopathic | Type: HUMAN OTC DRUG LABEL
Date: 20250303

ACTIVE INGREDIENTS: PRUNUS LAUROCERASUS LEAF 30 [hp_C]/30 [hp_C]; SELENICEREUS GRANDIFLORUS STEM 30 [hp_C]/30 [hp_C]; CRATAEGUS LAEVIGATA WHOLE 30 [hp_C]/30 [hp_C]; CONVALLARIA MAJALIS 30 [hp_C]/30 [hp_C]; ADONIS VERNALIS WHOLE 30 [hp_C]/30 [hp_C]; IBERIS AMARA SEED 30 [hp_C]/30 [hp_C]; VISCUM ALBUM FRUITING TOP 30 [hp_C]/30 [hp_C]
INACTIVE INGREDIENTS: ALCOHOL 30 [hp_C]/30 [hp_C]

BM216

DOSAGE AND ADMINISTRATION

How to Use

Mix with half a cup of water 3-4 times per day. Ages 12 or older, 10 drops. Ages 12-2, 5 drops. Ages 2 and under, consult your Doctor.

Inactive:

Alcohol Base to Preserve Product

ACTIVE INGREDIENTS

Adonis ver D7+20C 0.10mL each (HPUS), Cactus grand D2+20C 0.10mL each (HPUS), Convallaria D7+20C 0.10mL each (HPUS), Crataegus oxy D2+20C 0.10mL each (HPUS), Iberis amara D4+40C 0.10mL each (HPUS), Laurocerasus D4+40C 0.10mL each (HPUS), Viscum alb D3+30C 0.10mL each (HPUS)

KEEP OUT OF REACH OF CHILDREN

Warnings and Storage:

Ask a professional before use if pregnant or breastfeeding or if you have severe symptoms.

Keep away from children. If you have a reaction to this product that is not positive, discontinue use. Store in a cool and dry place

*CLAIMS BASED ON TRADITIONAL HOMEOPATHIC PRACTICE, NOT ACCEPTED MEDICAL EVIDENCE NOT FDA EVALUATED.
This product is not intended to diagnose, treat, cure, or prevent any disease.

Warnings and Storage:

Ask a professional before use if pregnant or breastfeeding or if you have severe symptoms.

Keep away from children. If you have a reaction to this product that is not positive, discontinue use. Store in a cool and dry place

*CLAIMS BASED ON TRADITIONAL HOMEOPATHIC PRACTICE, NOT ACCEPTED MEDICAL EVIDENCE NOT FDA EVALUATED.
This product is not intended to diagnose, treat, cure, or prevent any disease.

Uses
Temporarily relieves occasional internal swelling and supports easier breathing.*

Uses
Temporarily relieves occasional internal swelling and supports easier breathing.*

Entire package label